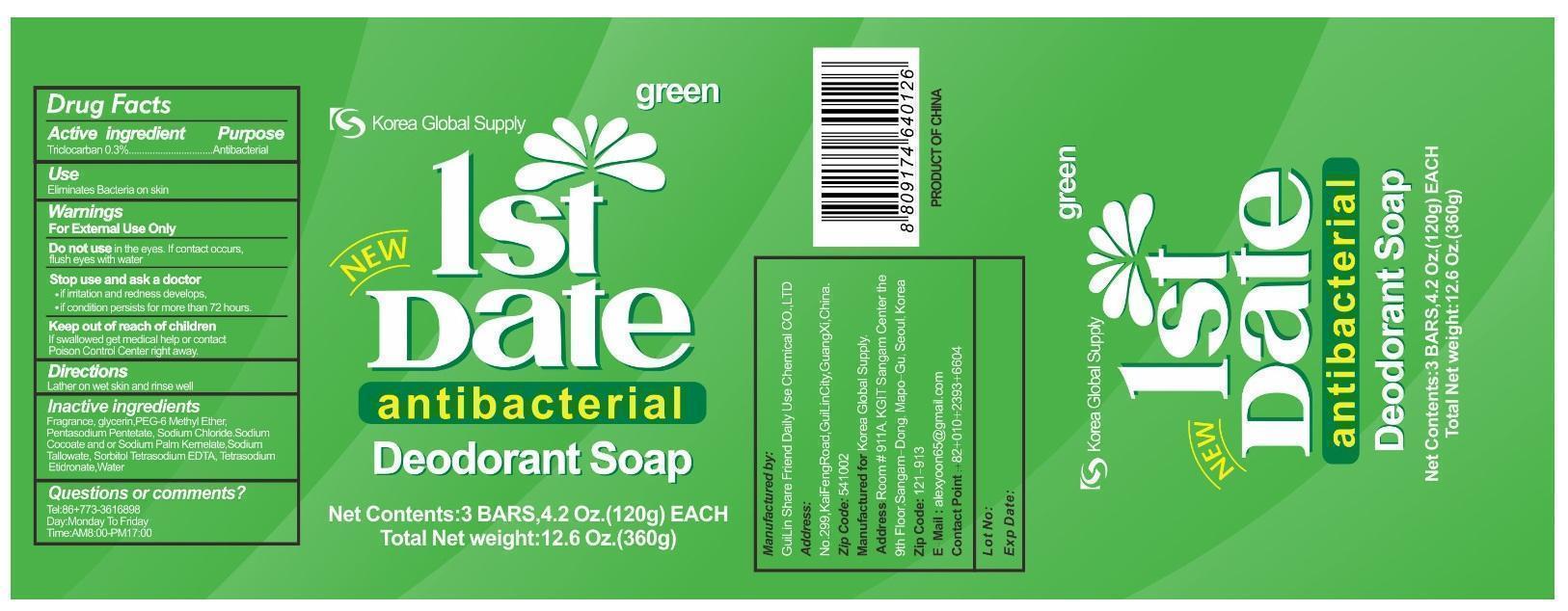 DRUG LABEL: 1st Date antibacterial Deodorant (Green)
NDC: 70012-103 | Form: SOAP
Manufacturer: Guilin Share Friend Daily Use Chemical Co.,Ltd
Category: otc | Type: HUMAN OTC DRUG LABEL
Date: 20150902

ACTIVE INGREDIENTS: TRICLOCARBAN 0.3 g/100 g
INACTIVE INGREDIENTS: GLYCERIN; PEG-6 METHYL ETHER; PENTASODIUM PENTETATE; SODIUM CHLORIDE; SODIUM COCOATE; SODIUM PALM KERNELATE; SODIUM TALLOWATE, BEEF; SORBITOL; EDETATE SODIUM; ETIDRONATE TETRASODIUM; WATER

1st Date antibacterial Deodorant Soap (Green)

Active ingredient

Triclocarban 0.3%

Purpose

Antibacterial

Keep out of reach of children

If swallowed get medical help or contact Poison Control Center right away.

Use

Eliminates Bacteria on skin

Warnings

For External Use Only

Do not use in the eyes. If contact occurs, flush eyes with water

Stop use and ask a doctor

- if irritation and redness develops,
- if condition persists for more than 72 hours.

Directions

Lather on wet skin and rinse well

Inactive ingredients

Fragrance, glycerin, PEG-6 Methyl Ether, Pentasodium Pentetate, Sodium Chloride, Sodium Cocoate and or Sodium Palm Kernelate, Sodium Tallowate, Sorbitol, Tetrasodium EDTA, Tetrasodium Etidronate, Water

Questions or comments?

Tel: 86+773-3616898

Day: Monday To Friday

Time: AM8:00-PM17:00

Manufactured by:

GuiLin Share Friend Daily Use Chemical CO., LTD

Address:

No.299, KaiFengRoad, GuiLinCity,GuangXi, China.

Zip Code: 541002

Manufactured for Korea Global Supply.

Address:Room #911A, KGIT Sangam Center the 9th Floor, Sangam-Dong, Mapo-Gu, Seoul, Korea

Zip Code: 121-913

E-Mail : alexyoon65@gmail.com

Contact Point:+82+010+2393+6604